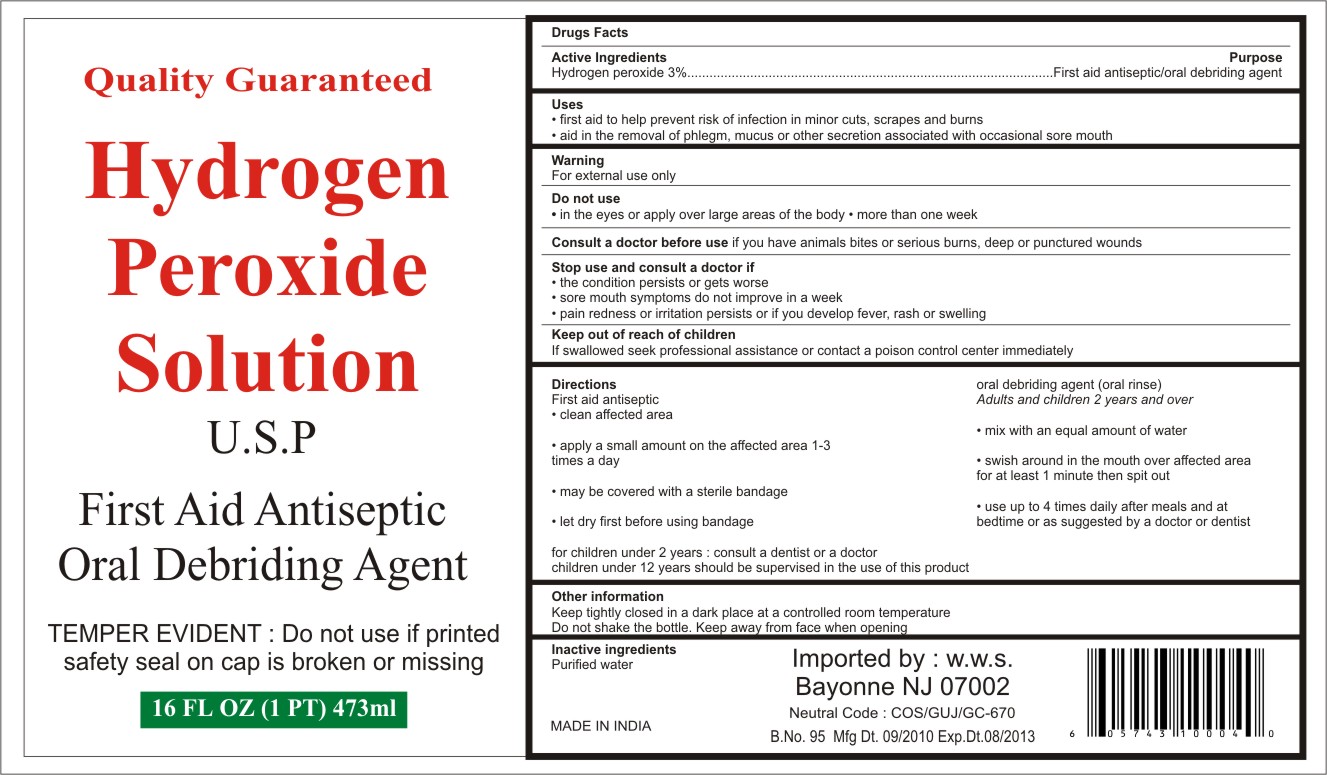 DRUG LABEL: Hydrogen Peroxide
                        
NDC: 76384-007 | Form: SOLUTION
Manufacturer: Worldwide Sales & Distribution Corp.
Category: otc | Type: HUMAN OTC DRUG LABEL
Date: 20110825

ACTIVE INGREDIENTS: HYDROGEN PEROXIDE .3 kg/100 L
INACTIVE INGREDIENTS: WATER

Quality Guaranteed Hydrogen Peroxide Solution

Drug Facts

Active ingredient
Hydrogen peroxide 3%

Purpose
First aid antiseptic
Oral debriding agent

Uses

- first aid to help prevent the risk of infection in minor cuts, scrapes and burns
- aid in the removal of phlegm, mucus or other secretions associated with occasional sore mouth

Warnings
For external use only

Do not use

- in the eyes or apply over large areas of the body
- more than one week

ASK DOCTOR

Consult a doctor before use if you have animal bites or serious burns, deep or punctured wounds

Stop use and ask a doctor if

- the condition persists or gets worse
- sore mouth symptoms do not improve in a week
- pain redness or irritation persists or if you develop fever, rash or swelling

Keep out of reach of children
If swallowed seek professional assistance or contact a poison control center immediately

Directions
First aid antiseptic
•clean the affected area
•apply a small amount of product on the affected area 1 to 3 times a day
•may be covered with a sterile bandage
•let dry first before using bandage
Oral debriding agent (oral rinse)
Adults and children 2 years of age and over:
• mix with equal amount of water
• swish around in the mouth over the affected area for at least 1 minute and then spit out
• use up to 4 times daily after meals and at bedtime or as directed by a doctor or dentist
• children under 2 years of age: consult a dentist or doctor
• children under 12 years of age should be supervised in the use of this product

Other information
Keep tightly closed in a dark place at controlled room temperature
Do not shake bottle. Keep away from face when opening

Inactive ingredient
Purified water